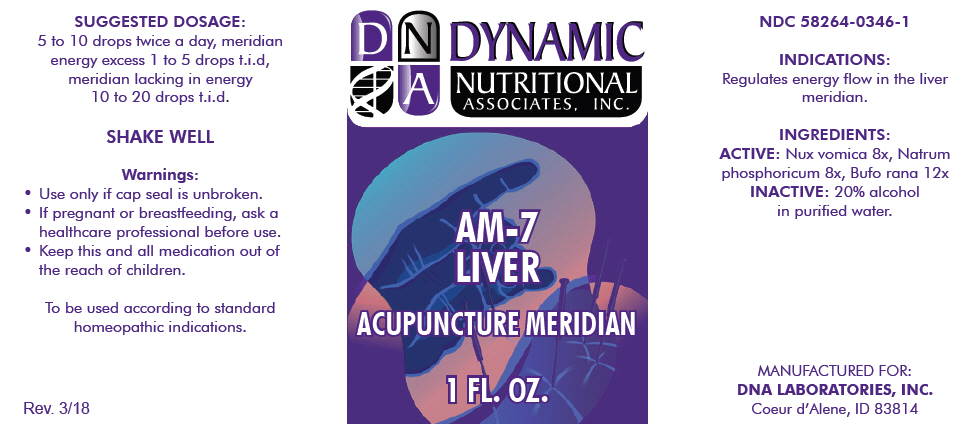 DRUG LABEL: AM-7
NDC: 58264-0346 | Form: SOLUTION
Manufacturer: DNA Labs, Inc.
Category: homeopathic | Type: HUMAN OTC DRUG LABEL
Date: 20250109

ACTIVE INGREDIENTS: STRYCHNOS NUX-VOMICA SEED 8 [hp_X]/1 mL; SODIUM PHOSPHATE, DIBASIC, HEPTAHYDRATE 8 [hp_X]/1 mL; BUFO BUFO WHOLE 12 [hp_X]/1 mL
INACTIVE INGREDIENTS: ALCOHOL; WATER

AM-7

NDC 58264-0346-1

INDICATIONS

PURPOSE

Regulates energy flow in the liver meridian.

INGREDIENTS

ACTIVE

Nux vomica 8x, Natrum phosphoricum 8x, Bufo rana 12x

INACTIVE

20% alcohol in purified water.

SUGGESTED DOSAGE

5 to 10 drops twice a day, meridian energy excess 1 to 5 drops t.i.d, meridian lacking in energy 10 to 20 drops t.i.d.

STORAGE AND HANDLING

SHAKE WELL

Warnings

- Use only if cap seal is unbroken.

PREGNANCY OR BREAST FEEDING

- If pregnant or breastfeeding, ask a healthcare professional before use.

KEEP OUT OF REACH OF CHILDREN

- Keep this and all medication out of the reach of children.

To be used according to standard homeopathic indications.

PRINCIPAL DISPLAY PANEL - 1 FL. OZ. Bottle Label

DYNAMIC
NUTRITIONAL
ASSOCIATES, INC.

AM-7
LIVER

ACUPUNCTURE MERIDIAN

1 FL. OZ.